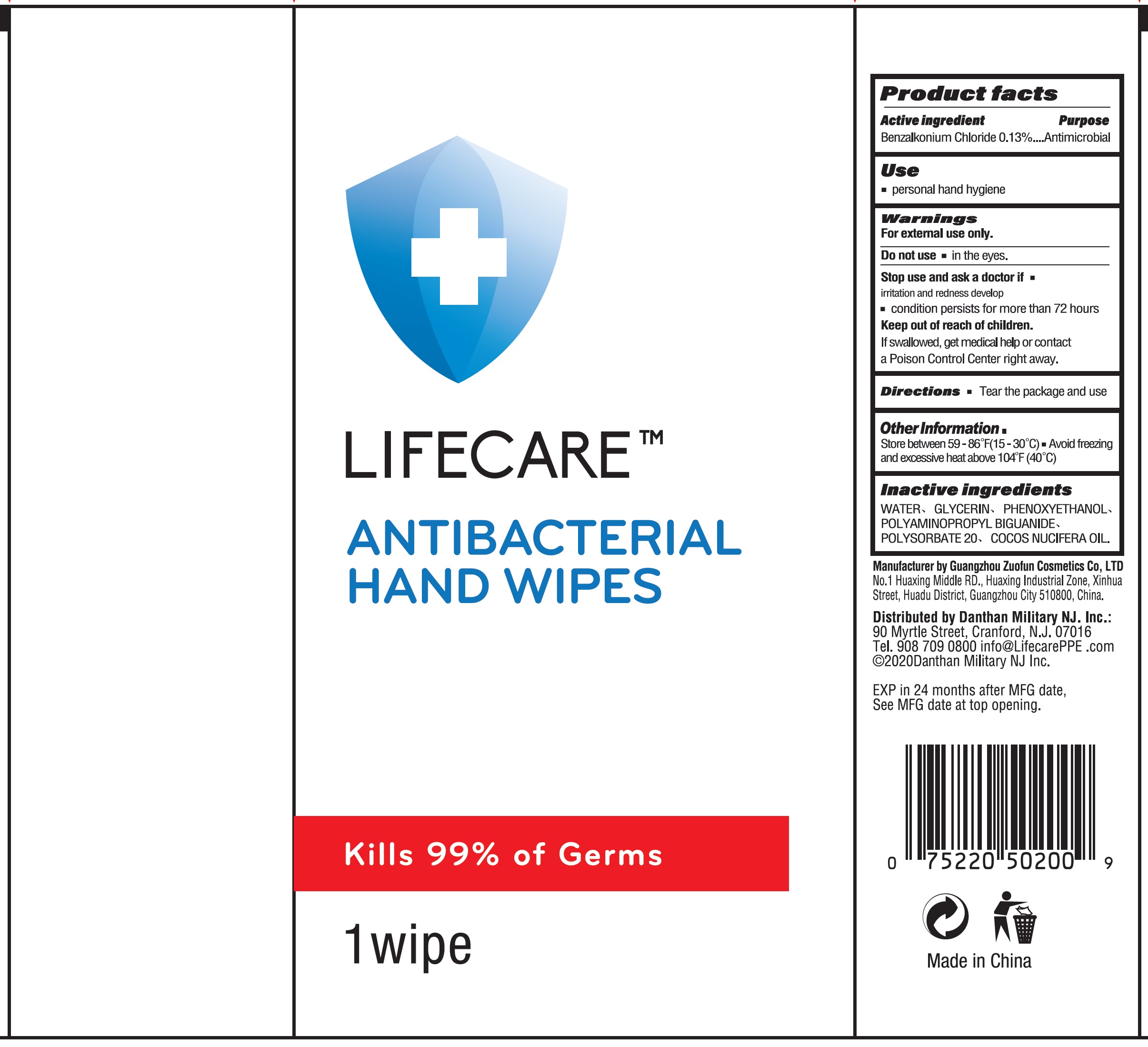 DRUG LABEL: Lifecare Antibacterial Hand Wipes
NDC: 80044-011 | Form: CLOTH
Manufacturer: Danthan Military NJ Inc.
Category: otc | Type: HUMAN OTC DRUG LABEL
Date: 20201124

ACTIVE INGREDIENTS: BENZALKONIUM CHLORIDE 1.3 mg/1 mL
INACTIVE INGREDIENTS: WATER; GLYCERIN; PHENOXYETHANOL; POLYAMINOPROPYL BIGUANIDE; POLYSORBATE 20; COCOS NUCIFERA WHOLE

Lifecare Antibacterial Hand Wipes

Active ingredient

Benzalkonium Chloride 0.13%

Purpose

Antimicrobial

Use

- personal hand hygiene

Warnings

For external use only.

Do not use

- in the eyes.

Stop use and ask a doctor if

- irritation and redness develop
- condition persists for more than 72 hours

Keep out of reach of children.

If swallowed, get medical help or contact a Poison Control Center right away.

Directions

- Tear the package and use

Other Information

- Store between 59-86°F (15-30°C)
- Avoid freezing and excessive heat above 104°F (40°C)

Inactive ingredients

WATER, GLYCERIN, PHENOXYETHANOL, POLYAMINOPROPYL BIGUANIDE, POLYSORBATE 20, COCO NUCIFERA OIL.